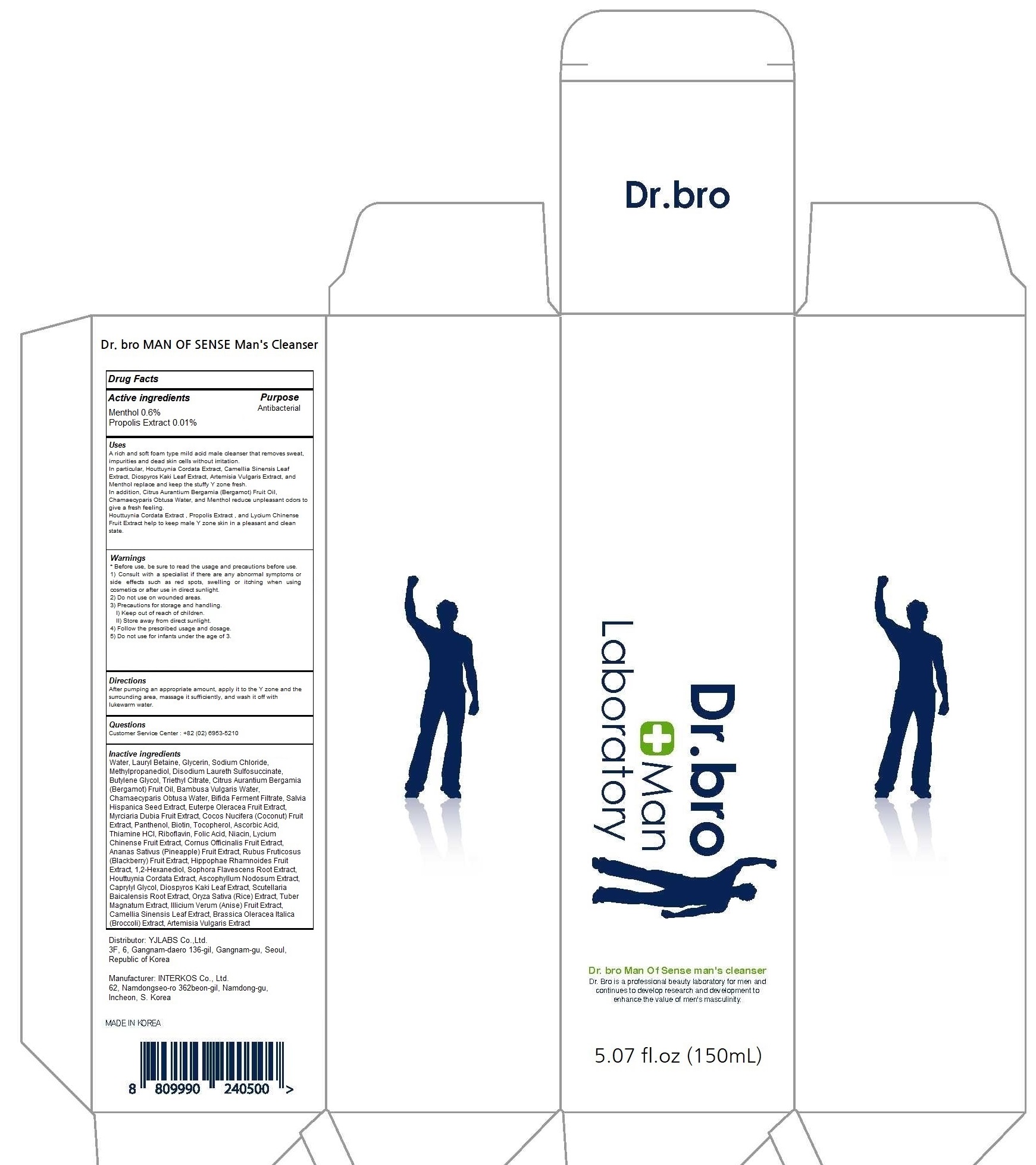 DRUG LABEL: Dr.bro MAN OF SENSE Mans Cleanser
NDC: 81168-010 | Form: LIQUID
Manufacturer: YJLabs Co., Ltd.
Category: otc | Type: HUMAN OTC DRUG LABEL
Date: 20201125

ACTIVE INGREDIENTS: Menthol 0.9 g/150 mL; PROPOLIS WAX 0.015 g/150 mL
INACTIVE INGREDIENTS: Water; Glycerin; Sodium Chloride

Dr.bro MAN OF SENSE Man’s Cleanser

ACTIVE INGREDIENTS

Menthol 0.6%
Propolis Extract 0.01%

INACTIVE INGREDIENTS

Water, Lauryl Betaine, Glycerin, Sodium Chloride, Methylpropanediol, Disodium Laureth Sulfosuccinate, Butylene Glycol, Triethyl Citrate, Citrus Aurantium Bergamia (Bergamot) Fruit Oil, Bambusa Vulgaris Water, Chamaecyparis Obtusa Water, Bifida Ferment Filtrate, Salvia Hispanica Seed Extract, Euterpe Oleracea Fruit Extract, Myrciaria Dubia Fruit Extract, Cocos Nucifera (Coconut) Fruit Extract, Panthenol, Biotin, Tocopherol, Ascorbic Acid, Thiamine HCl, Riboflavin, Folic Acid, Niacin, Lycium Chinense Fruit Extract, Cornus Officinalis Fruit Extract, Ananas Sativus (Pineapple) Fruit Extract, Rubus Fruticosus (Blackberry) Fruit Extract, Hippophae Rhamnoides Fruit Extract, 1,2-Hexanediol, Sophora Flavescens Root Extract, Houttuynia Cordata Extract, Ascophyllum Nodosum Extract, Caprylyl Glycol, Diospyros Kaki Leaf Extract, Scutellaria Baicalensis Root Extract, Oryza Sativa (Rice) Extract, Tuber Magnatum Extract, Illicium Verum (Anise) Fruit Extract, Camellia Sinensis Leaf Extract, Brassica Oleracea Italica (Broccoli) Extract, Artemisia Vulgaris Extract

PURPOSE

Antibacterial

WARNINGS

Before use, be sure to read the usage and precautions before use.
1) Consult with a specialist if there are any abnormal symptoms or side effects such as red spots, swelling or itching when using cosmetics or after use in direct sunlight.
2) Do not use on wounded areas.
3) Precautions for storage and handling.
I) Keep out of reach of children.
II) Store away from direct sunlight.
4) Follow the prescribed usage and dosage.
5) Do not use for infants under the age of 3.

KEEP OUT OF REACH OF CHILDREN

Uses

A rich and soft foam type mild acid male cleanser that removes sweat, impurities and dead skin cells without irritation.
In particular, Houttuynia Cordata Extract, Camellia Sinensis Leaf Extract, Diospyros Kaki Leaf Extract, Artemisia Vulgaris Extract, and Menthol replace and keep the stuffy Y zone fresh.
In addition, Citrus Aurantium Bergamia (Bergamot) Fruit Oil, Chamaecyparis Obtusa Water, and Menthol reduce unpleasant odors to give a fresh feeling.
Houttuynia Cordata Extract , Propolis Extract , and Lycium Chinense Fruit Extract help to keep male Y zone skin in a pleasant and clean state.

Directions

After pumping an appropriate amount, apply it to the Y zone and the surrounding area, massage it sufficiently, and wash it off with lukewarm water.

QUESTIONS

Customer Service Center : +82 (02) 6953-5210